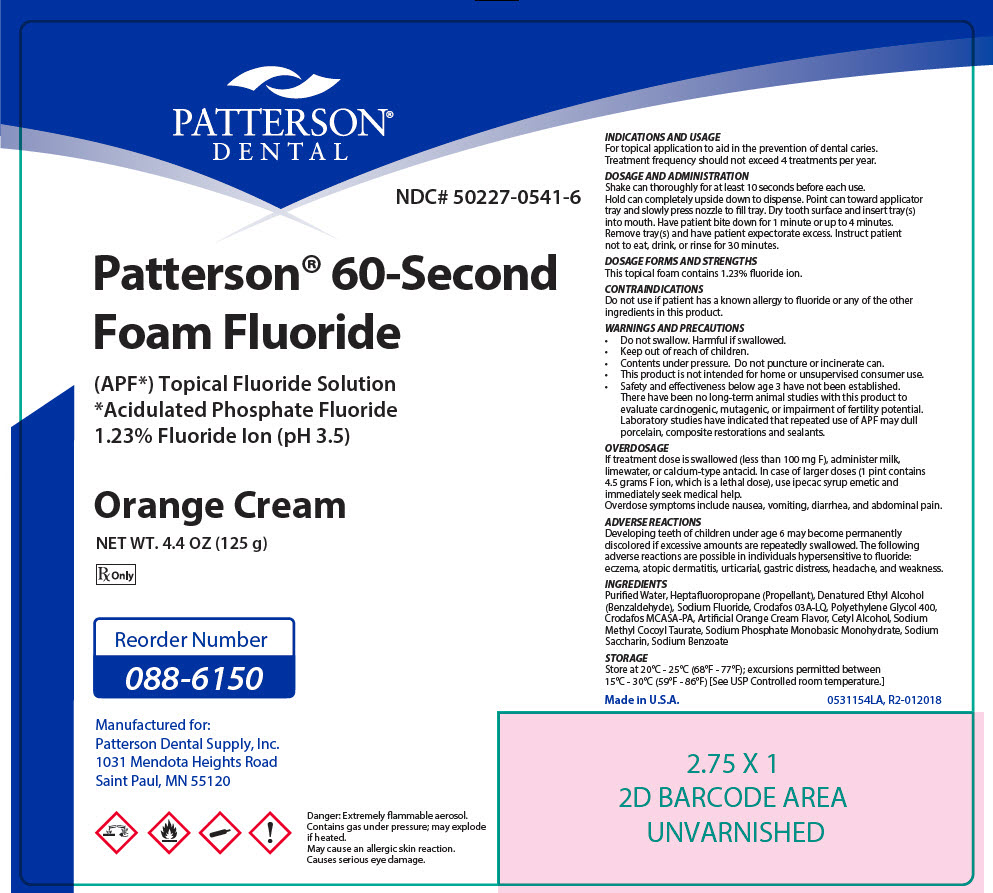 DRUG LABEL: Topical 60 Sec Sodium Fluoride 
NDC: 50227-0541 | Form: AEROSOL, FOAM
Manufacturer: Patterson Dental Supply Inc
Category: prescription | Type: HUMAN PRESCRIPTION DRUG LABEL
Date: 20181221

ACTIVE INGREDIENTS: Sodium Fluoride 123 mg/1 g
INACTIVE INGREDIENTS: SACCHARIN SODIUM; Sodium Benzoate; Sodium Methyl Cocoyl Taurate; Polyethylene Glycol 400; Cetyl Phosphate; Cetyl Alcohol; Oleth-3 Phosphate; Sodium Phosphate, Monobasic, Monohydrate; Apaflurane; Benzaldehyde

Patterson® 60-Second Foam Fluoride Orange Cream

INDICATIONS AND USAGE

For topical application to aid in the prevention of dental caries.

Treatment frequency should not exceed 4 treatments per year.

DOSAGE AND ADMINISTRATION

Shake can thoroughly for at least 10 seconds before each use.

Hold can completely upside down to dispense. Point can toward applicator tray and slowly press nozzle to fill tray. Dry tooth surface and insert tray(s) into mouth. Have patient bite down for 1 minute or up to 4 minutes.

Remove tray(s) and have patient expectorate excess. Instruct patient not to eat, drink, or rinse for 30 minutes.

DOSAGE FORMS AND STRENGTHS

This topical foam contains 1.23% fluoride ion.

CONTRAINDICATIONS

Do not use if patient has a known allergy to fluoride or any of the other ingredients in this product.

WARNINGS AND PRECAUTIONS

- Do not swallow. Harmful if swallowed.
- Keep out of reach of children.
- Contents under pressure. Do not puncture or incinerate can.
- This product is not intended for home or unsupervised consumer use.
- Safety and effectiveness below age 3 have not been established.
  There have been no long-term animal studies with this product to evaluate carcinogenic, mutagenic, or impairment of fertility potential.
  Laboratory studies have indicated that repeated use of APF may dull porcelain, composite restorations and sealants.

OVERDOSAGE

If treatment dose is swallowed (less than 100 mg F), administer milk, limewater, or calcium-type antacid. In case of larger doses (1 pint contains 4.5 grams F ion, which is a lethal dose), use ipecac syrup emetic and immediately seek medical help.

Overdose symptoms include nausea, vomiting, diarrhea, and abdominal pain.

ADVERSE REACTIONS

Developing teeth of children under age 6 may become permanently discolored if excessive amounts are repeatedly swallowed. The following adverse reactions are possible in individuals hypersensitive to fluoride: eczema, atopic dermatitis, urticarial, gastric distress, headache, and weakness.

INGREDIENTS

Purified Water, Heptafluoropropane (Propellant), Denatured Ethyl Alcohol (Benzaldehyde), Sodium Fluoride, Crodafos 03A-LQ, Polyethylene Glycol 400, Crodafos MCASA-PA, Artificial Orange Cream Flavor, Cetyl Alcohol, Sodium Methyl Cocoyl Taurate, Sodium Phosphate Monobasic Monohydrate, Sodium Saccharin, Sodium Benzoate

STORAGE

Store at 20°C - 25°C (68°F - 77°F); excursions permitted between 15°C - 30°C (59°F - 86°F) [See USP Controlled room temperature.]

Made in U.S.A.
0531154LA, R2-012018

PRINCIPAL DISPLAY PANEL - 125 g Canister Label

PATTERSON®
DENTAL

NDC# 50227-0541-6

Patterson® 60-Second
Foam Fluoride

(APF*) Topical Fluoride Solution
*Acidulated Phosphate Fluoride
1.23% Fluoride Ion (pH 3.5)

Orange Cream

NET WT. 4.4 OZ (125 g)

Rx Only

Reorder Number
088-6150

Manufactured for:
Patterson Dental Supply, Inc.
1031 Mendota Heights Road
Saint Paul, MN 55120

!

Danger: Extremely flammable aerosol.
Contains gas under pressure; may explode
if heated.
May cause an allergic skin reaction.
Causes serious eye damage.